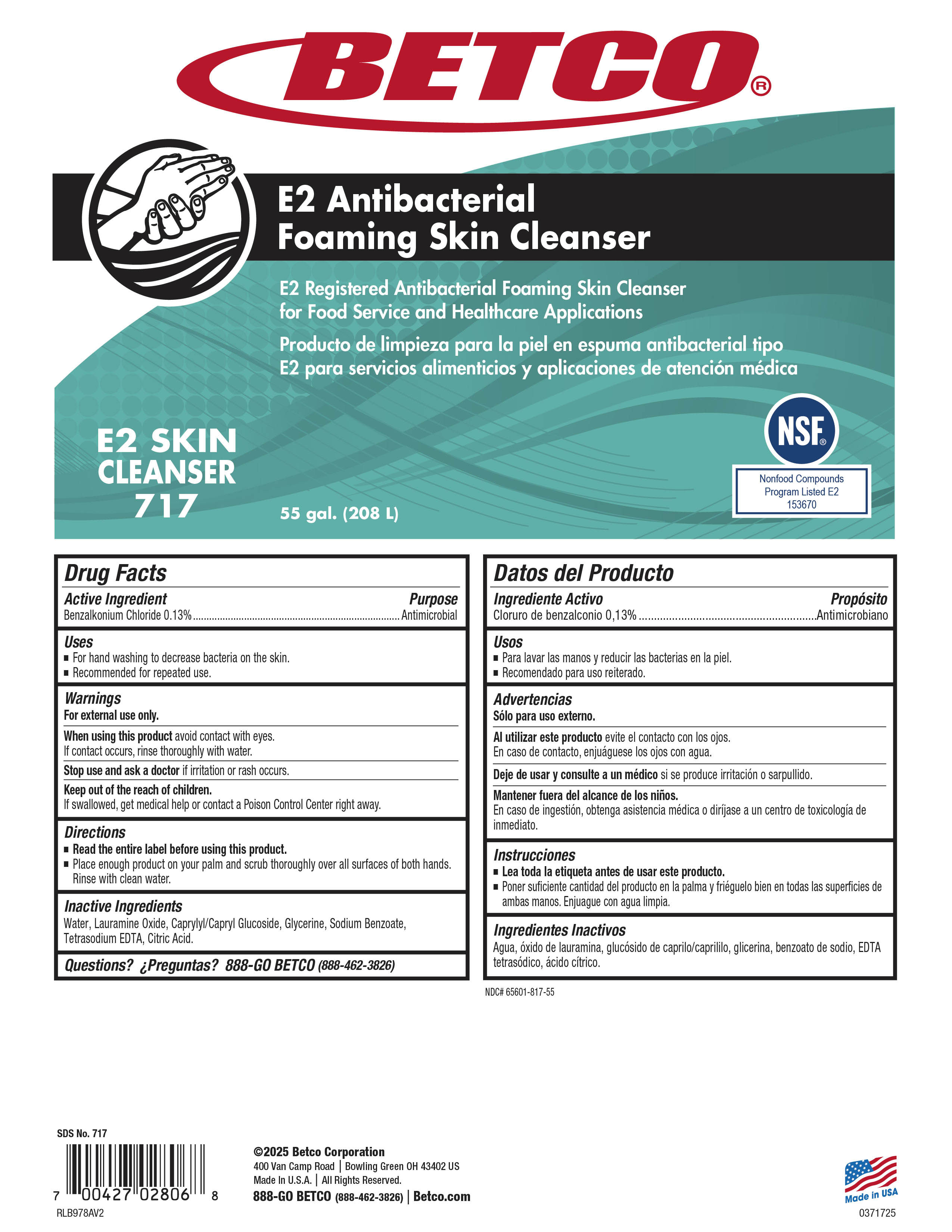 DRUG LABEL: E2 Antibacterial Foaming Skin Cleanser
NDC: 65601-817 | Form: SOAP
Manufacturer: Betco Corporation, Ltd.
Category: otc | Type: HUMAN OTC DRUG LABEL
Date: 20250320

ACTIVE INGREDIENTS: BENZALKONIUM CHLORIDE 1.3 mg/1 mL
INACTIVE INGREDIENTS: GLYCERIN; CAPRYLYL/CAPRYL OLIGOGLUCOSIDE; ANHYDROUS CITRIC ACID; WATER; LAURTRIMONIUM CHLORIDE; TETRASODIUM EDTA; ALCOHOL; SODIUM BENZOATE

E2 Antibacterial Foaming Skin Cleanser

E2 Antibacterial Foaming Skin Cleanser

Active Ingredient

Benzalkonium Chloride 0.13%

E2 Antibacterial Foaming Skin Cleanser

Uses

- For handwashing to decrease the bacteria on the skin.
- Recommended for repeated use.

E2 Antibacterial Foaming Skin Cleanser

Warnings

- For external use only.
- When using this product avoid contact with eyes. In case of contact flush with water
- Discontinue use is irritation or redness develops.
- Stop use and ask a doctor If irritation persists for more than 72 hours, or if condition persists for more than 72 hours.
- KEEP OUT OF REACH OF CHILDREN.
- If swallowed, get medical help or contact Poison Control Center right away.

E2 Antibacterial Foaming Skin Cleanser

Directions

- Read the entire label before using this product.
- Dispense 2 pumps of product in hands and scrub thoroughly over all surfaces of both hands for 15 seconds. Rinse with clean water.

E2 Antibacterial Foaming Skin Cleanser

Inactive Ingredients

Water, coco-glucoside, laurtrimonium chloride, cocamidopropylamine oxide, citric acid.

E2 Antibacterial Foaming Skin Cleanser

Purpose

Antimicrobial

E2 Antibacterial Foaming Skin Cleanser

KEEP OUT OF REACH OF CHILDREN